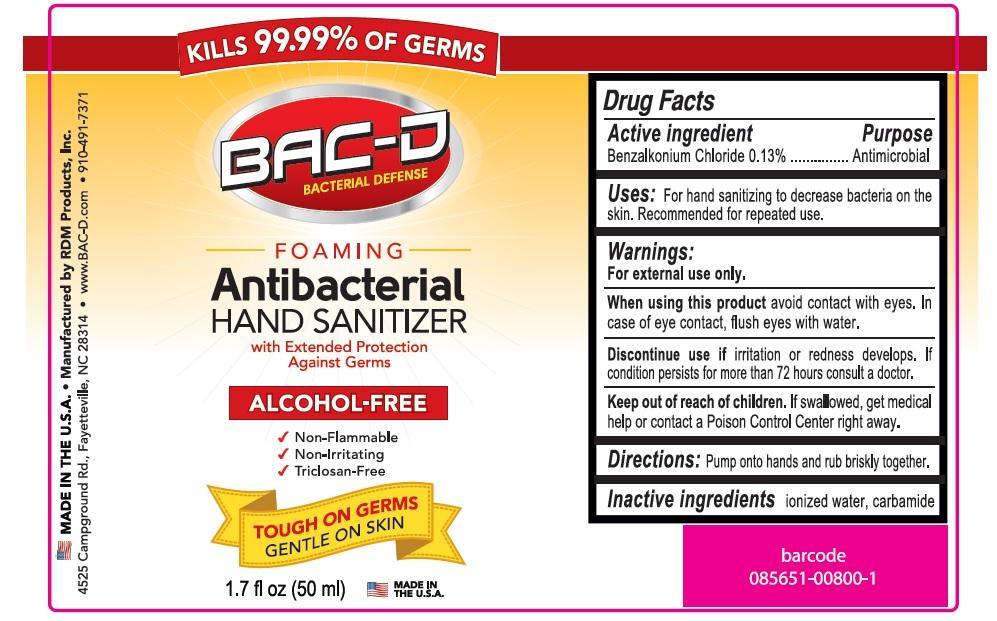 DRUG LABEL: BAC-D Foaming Antibacterial Hand sanitizer
NDC: 69082-600 | Form: LIQUID
Manufacturer: RDM Products, Inc
Category: otc | Type: HUMAN OTC DRUG LABEL
Date: 20151110

ACTIVE INGREDIENTS: BENZALKONIUM CHLORIDE 0.13 g/100 mL
INACTIVE INGREDIENTS: WATER; UREA

BAC-D Foaming Antibacterial Hand sanitizer

Active ingredient

Benzalkonium chloride 0.13 %

Purpose

Antimicrobial

Keep out of reach of children.

If swallowed, get medical help or contact a Poison Control Center right away.

Uses

- decrease bacteria and sanitizes skin
- recommended for repeated use

Warnings

For external use only.

When using this product avoid contact with eyes. In case of eye contact, flush eyes with water .

Stop use and ask a doctor if irritation or redness develops or if condition persists for more than 72 hours

Directions

- pump a small amount of foam in to palm of hand
- rub thoroughly over all surface of both hands
- rub hands together briskly until dry.

Inactive ingredients

Ionized water, Carbamide

Made in the U.S.A

Manufactured for

RDM Products Inc.

PO Box 35003

Fayetteville, NC 28303

910-491-7371

www.BAC-D.com